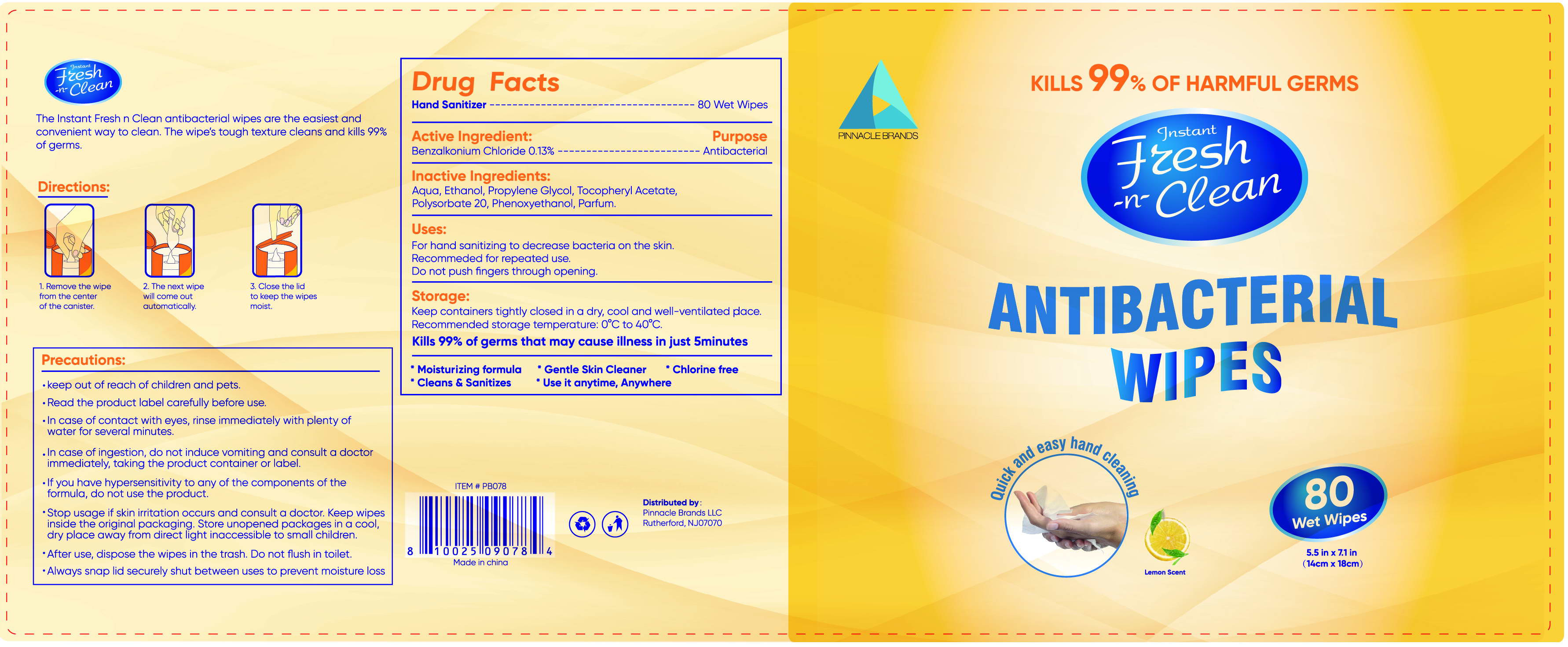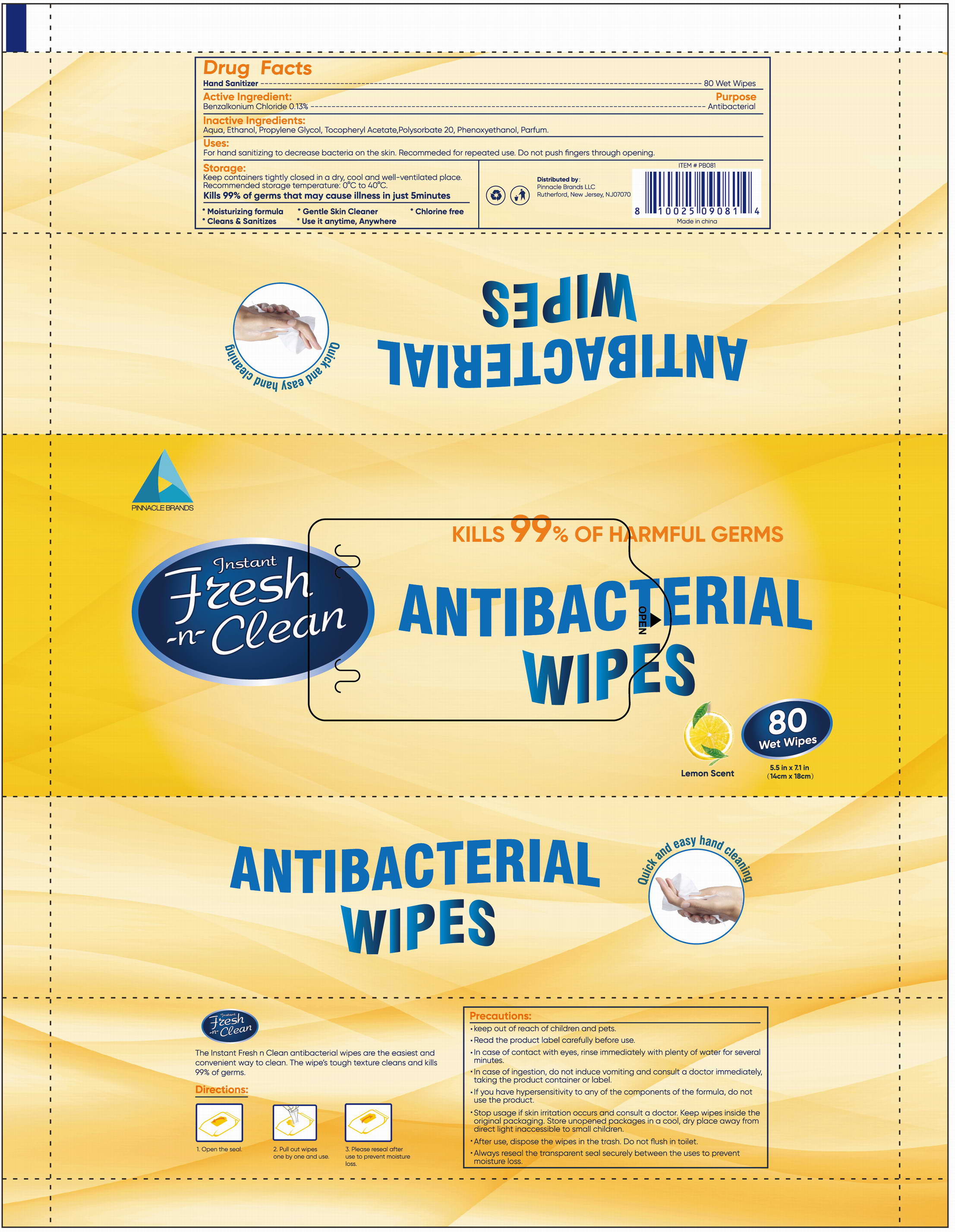 DRUG LABEL: Antibacterial Wet Wipes
NDC: 78183-006 | Form: CLOTH
Manufacturer: Kunming Ansheng Industry & Trade Co., Ltd.
Category: otc | Type: HUMAN OTC DRUG LABEL
Date: 20200721

ACTIVE INGREDIENTS: BENZALKONIUM CHLORIDE 0.13 U/100 U
INACTIVE INGREDIENTS: WATER; ALCOHOL 10 U/100 U; POLYSORBATE 20 0.05 U/100 U; PHENOXYETHANOL 0.1 U/100 U; PROPYLENE GLYCOL 0.1 U/100 U; ALPHA-TOCOPHEROL ACETATE 0.05 U/100 U

Antibacterial Wet Wipes (0.13%)

Active Ingredient(s)

Benzalkonium Chloride 0.13% v/v;

Purpose

Antibacterial; Kill 99% of germs that may cause illness in just 5 minutes;

Use

• For hand washing to decrease bacteria on the skin.
• Recommended for repeated use.
• Do not push fingers through opening.

Warnings

For external use only. Read the product label carefully before use.

Do not use

- on infants less than 2 months of age
- on open skin wounds
- If you have hypersensitivity to any of the components of the formula, do not use the product.

When using this product keep out of eyes, ears, and mouth.

In case of contact with eyes, rinse immediately with plenty of water for several minuter;

In case of ingestion, do not induce vomiting and consult a doctor immediately, taking the product container or label.

STOP USE

Stop usage if skin irritation occurs and consult a doctor.

Keep out of reach of children and pets.

Directions

Directions (For bag package)

• After use, dispose the wipes in the trash. Do not flush in toilet.
• Always reseal the transparent seal securely between the uses to

Directions (For Canister package)

• Remove the wipe from the center of the canister.

• The next wipe will come out automatically.

• Close the lid to keep the wipes moist.

Other information

- Keep containers tightly closed in a cool, dry place and well-ventilated place.
- Recommended Store temperature: 0℃ to 40℃
- Keep wipes inside the original packaging.
- Store unopened packages in a cool, dry place away from direct light inaccessible to small children.

Inactive ingredients

Aqua, Ethanol, Propylene Glycol, Tocopheryl Acetate, Polysorbate 20, Phenoxyethanol, Parfum

Package Label - Principal Display Panel

80 wipes in 1 bag; NDC: 78183-006-01;

80 wipes in 1 canister；NDC: 78183-006-02；